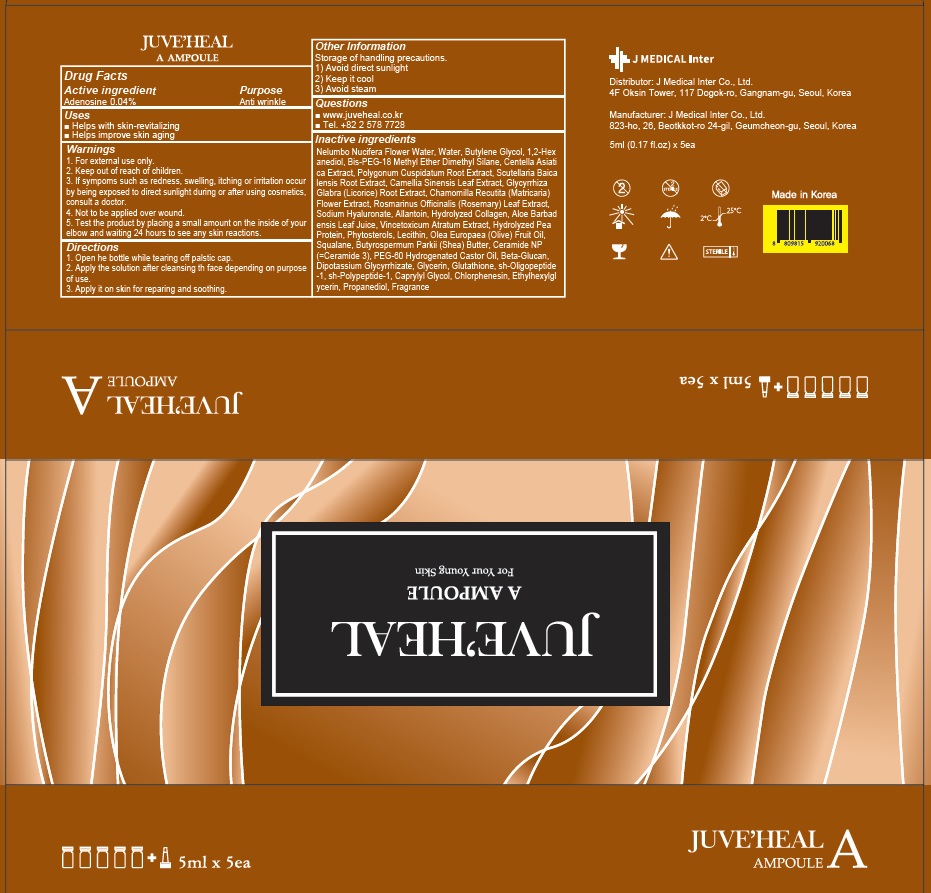 DRUG LABEL: JUVEHEAL A Ampoule
NDC: 81689-040 | Form: LIQUID
Manufacturer: J MEDICAL Inter Co., Ltd.
Category: otc | Type: HUMAN OTC DRUG LABEL
Date: 20210621

ACTIVE INGREDIENTS: Adenosine 0.04 g/100 mL
INACTIVE INGREDIENTS: NELUMBO NUCIFERA FLOWER OIL; Water; Butylene Glycol

ACTIVE INGREDIENT

Adenosine 0.04%

INACTIVE INGREDIENTS

Nelumbo Nucifera Flower Water, Water, Butylene Glycol, 1,2-Hexanediol, Bis-PEG-18 Methyl Ether Dimethyl Silane, Centella Asiatica Extract, Polygonum Cuspidatum Root Extract, Scutellaria Baicalensis Root Extract, Camellia Sinensis Leaf Extract, Glycyrrhiza Glabra (Licorice) Root Extract, Chamomilla Recutita (Matricaria) Flower Extract, Rosmarinus Officinalis (Rosemary) Leaf Extract, Sodium Hyaluronate, Allantoin, Hydrolyzed Collagen, Aloe Barbadensis Leaf Juice, Vincetoxicum Atratum Extract, Hydrolyzed Pea Protein, Phytosterols, Lecithin, Olea Europaea (Olive) Fruit Oil, Squalane, Butyrospermum Parkii (Shea) Butter, Ceramide NP (=Ceramide 3), PEG-60 Hydrogenated Castor Oil, Beta-Glucan, Dipotassium Glycyrrhizate, Glycerin, Glutathione, sh-Oligopeptide-1, sh-Polypeptide-1, Caprylyl Glycol, Chlorphenesin, Ethylhexylglycerin, Propanediol, Fragrance

PURPOSE

Anti wrinkle

WARNINGS

1. For external use only
2. Keep out of reach of children
3. If sympoms such as redness, swelling, itching or irritation occur by being exposed to direct sunlight during or after using cosmetics, consult a doctor.
4. Not to be applied over wound
5. Test the product by placing a small amount on the inside of your elbow and waiting 24 hours to see any skin reactions.

KEEP OUT OF REACH OF CHILDREN

Uses

■ Helps with skin-revitalizing
■ Helps improve skin aging

Directions

1. Open he bottle while tearing off palstic cap.
2. Apply the solution after cleansing th face depending on purpose of use.
3. Apply it on skin for reparing and soothing.

Other information

Storage of handling precautions.
1) Avoid direct sunlight
2) Keep it cool
3) Avoid steam

QUESTIONS

■ http://juveheal.co.kr/products.php
■ Tel. +82 2 578 7728